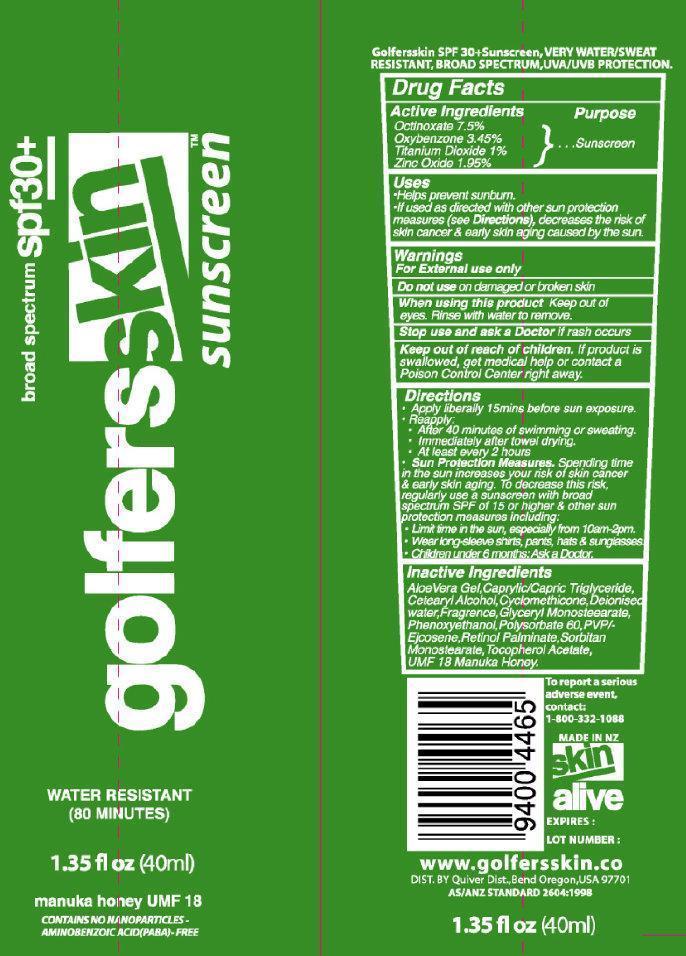 DRUG LABEL: Golfers Skin Broad Spectrum SPF 30 Plus Sunscreen
                
NDC: 75916-4020 | Form: CREAM
Manufacturer: Skin Alive, Ltd.
Category: otc | Type: HUMAN OTC DRUG LABEL
Date: 20150113

ACTIVE INGREDIENTS: OCTINOXATE 75 mg/1 mL; OXYBENZONE 34.5 mg/1 mL; TITANIUM DIOXIDE 10 mg/1 mL; ZINC OXIDE 19.5 mg/1 mL
INACTIVE INGREDIENTS: ALOE VERA LEAF; MEDIUM-CHAIN TRIGLYCERIDES; CETOSTEARYL ALCOHOL; CYCLOMETHICONE; WATER; GLYCERYL MONOSTEARATE; PHENOXYETHANOL; POLYSORBATE 60; VITAMIN A PALMITATE; SORBITAN MONOSTEARATE; ALPHA-TOCOPHEROL ACETATE; HONEY

Golfers Skin Broad Spectrum SPF 30+ Sunscreen

Active Ingredients

Octinoxate 7.5%

Oxybenzone 3.45%

Titanium Dioxide 1%

Zinc Oxide 1.95%

Purpose

Sunscreen

Uses

- Helps prevents sunburn
- If used as directed with other sun protection measures (see Directions), decreases the risk of skin cancer and early skin aging caused by the sun.

Warnings

For external use only

When using this product

Keep out of eyes. Rinse with water to remove.

Stop use and ask a doctor if

rash occurs

Keep out of reach of children

If product is swallowed, get medical help or contact a Poison Control Center right away.

Directions

Apply generously 15 mins before sun exposure.
Reapply:
* After 40 minutes of swimming or sweating.
* Immediately after towel drying
* At least every 2 hours
Sun Protections Measure. Spending time in the sun increases your risk of skin cancer and early skin aging. To decrease this risk, regularly use and sunscreen with broad spectrum SPF of 15 or higher and other sun protection measures including:
* Limit time in the sun, especially from 10am-2pm
* Wear long-sleeve shirts, pants, hats and sunglasses
* Children under 6 months: Ask a Doctor

Inactive Ingredients

Aloe Vera Gel, Caprylic/Capric Triglyceride, Cetearyl Alcohol, Cyclomethicone, Deionised Water, Fragrance, Glyceryl Monostearate, Phenoxyethanol, Polysorbate 60, PVP ejcosene, Retinol Palminate, Sorbitan Monostearate, Tocopherol Acetate, UMF 18 Manuka Honey

PACKAGE LABEL

spf 30+

very water/sweat resistant

broad spectrum

UVA/UVB Protection

Golfersskin Sunscreen

Proven in Extreme New Zealand conditions

manuka honey UMF 18

CONTAINS NO NANOPARTICLES - AMINOBENZOIC ACID (PABA)-FREE